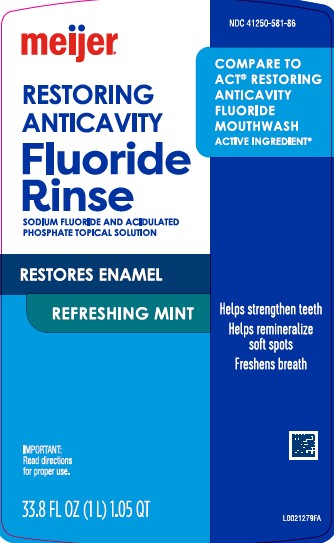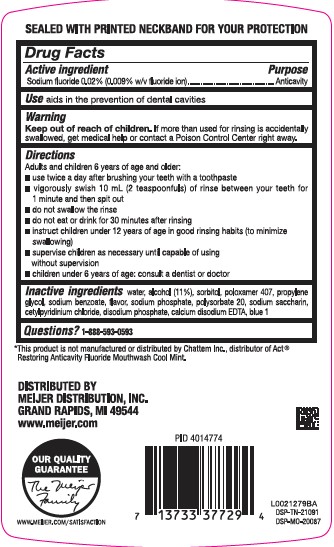 DRUG LABEL: Anticavity
NDC: 41250-581 | Form: MOUTHWASH
Manufacturer: Meijer, Inc.
Category: otc | Type: HUMAN OTC DRUG LABEL
Date: 20260219

ACTIVE INGREDIENTS: SODIUM FLUORIDE 0.2 mg/1 mL
INACTIVE INGREDIENTS: CETYLPYRIDINIUM CHLORIDE; SODIUM PHOSPHATE, DIBASIC, ANHYDROUS; EDETATE CALCIUM DISODIUM ANHYDROUS; FD&C BLUE NO. 1; WATER; ALCOHOL; SORBITOL; POLOXAMER 407; PROPYLENE GLYCOL; SODIUM BENZOATE; SODIUM PHOSPHATE; POLYSORBATE 20; SACCHARIN SODIUM

Meijer 581.000/581AA-AC
Restoring Anticavity Fluoride Mouthwash

Tamper Evident Statement

SEALED WITH PRINTED NECKBAND FOR YOUR PROTECTION

Active ingredient

Sodium fluoride 0.02% (0.009% w/v fluoride ion)

Purpose

Anticavity

Use

aids in the prevention of dental cavities

Warnings

For this product

Keep out of reach of children.

If more than used for rinsing is accidentally swallowed, get medical help or contact a Poison Control Center right away.

Directions

Adults and children 6 years of age and older:

- use twice a day after brushing your teeth with a toothpaste
- vigorously swish 10 mL (2 teaspoonfuls) of rinse between your teeth for 1 minute and then spit out
- do not swallow the rinse
- do not eat or drink for 30 minutes after rinsing
- instruct children under 12 years of age in good rinsing habits (to minimize swallowing)
- supervise children as necessary until capable of using without supervision
- children under 6 years of age: consult a dentist or doctor

Inactive ingredients

water, alcohol (11%), sorbitol, poloxamer 407, propylene glycol, sodium benzoate, flavor, sodium phosphate, polysorbate 20, sodium saccharin, cetylpyridinium chloride, disodium phosphate, calcium disodium EDTA, blue 1

Questions?

Call 1-888-593-0593

Disclaimer

*This product is not manufactured or distributed by Chattem, Inc., distributor of Act® Restoring Anticavity Fluoride Mouthwash Cool Mint.

ADVERSE REACTION

DISTRIBUTED BY

MEIJER DISTRIBUTION, INC.

GRAND RAPIDS, MI 49544

www.meijer.com

OUR QUALITY GUARANTEE

The Meijer Family

WWW.MEIJER.COM/sATISFACTION

DSP-TN-21091

DSP-MO-20087

Principal display panel

NDC 41250-581-86

meijer®

Compare to Act® Restoring Anticavity Fluoride Mouthwash Active Ingredient*

RESTORING ANTICAVITY

Fluoride Rinse

Sodium Fluoride And Acidulated Phosphate Topical Solution

RESTORES ENAMEL

Refreshing Mint

Helps strengthen teeth

Helps remineralize soft spots

Freshens breath

IMPORTANT: Read directions for proper use

33.8 FL OZ (1 L) 1.05 QT